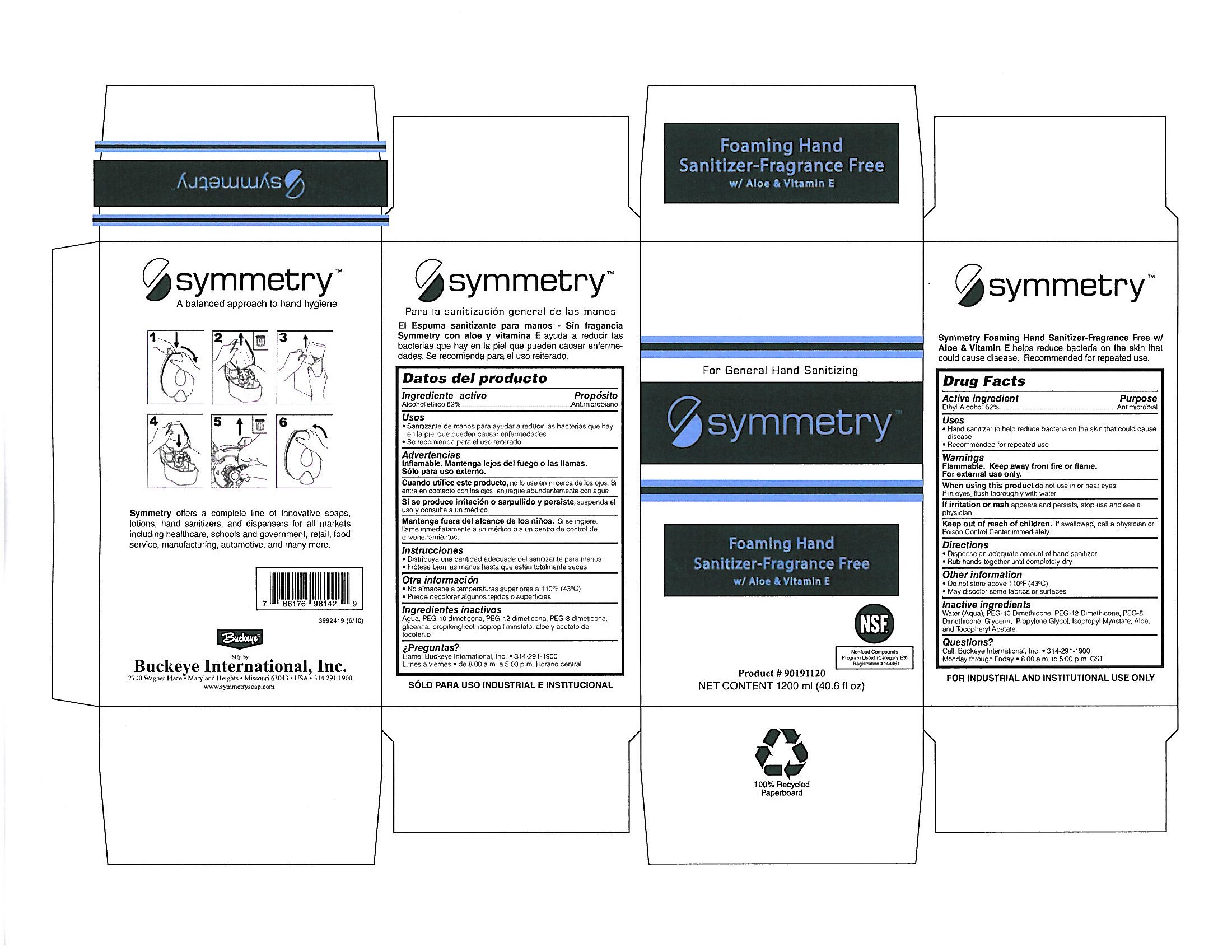 DRUG LABEL: Symmetry Foaming Hand Sanitizer-Fragrance Free with Aloe and Vitamin E
NDC: 30805-009 | Form: LIQUID
Manufacturer: Buckeye International, Inc.
Category: otc | Type: HUMAN OTC DRUG LABEL
Date: 20250325

ACTIVE INGREDIENTS: ALCOHOL 62 mL/100 mL
INACTIVE INGREDIENTS: WATER; GLYCERIN; PROPYLENE GLYCOL; ISOPROPYL MYRISTATE; ALOE; PEG-8 DIMETHICONE; ALPHA-TOCOPHEROL ACETATE; PEG-10 DIMETHICONE (600 CST); PEG-12 DIMETHICONE (300 CST)

Drug Facts 30805-009

Active Ingredient

Ethyl Alcohol 62%

Purpose

Antimicrobial

Uses

Hand sanitizer to help reduce bacteria on the skin that could cause disease

Recommended for repeated use

Warnings

Flammable. Keep away from fire or flame.

For external use only.

When using this product do not use in or near eyes.

If in eyes, flush thoroughly with water.

ADVERSE REACTIONS

If irritation or rash appears and persists, stop use and see a physician.

Keep out of reach of children. If swallowed, call a physician or Poison Control Center immediately.

Directions

Dispense an adequate amount of hand sanitizer

Rub hands together until completely dry

Other information

Do not store above 110 F (43 C)

May discolor some fabrics or surfaces

Inactive ingredients

Water (Aqua), PEG-10 Dimethicone, PEG-12 Dimethicone, PEG-8 Dimethicone, Glycerin, Propylene Glycol, Isopropyl Myristate, Aloe, and Tocopheryl Acetate.

Questions?

Call: Buckeye International, Inc. 314-291-1900

Monday through Friday 8:00 a.m. to 5:00 p.m. CST

PACKAGE LABEL

For General Hand Sanitizing

Symmetry

Foaming Hand

Sanitizer-Fragrance Free

w/ Aloe and Vitamin E

NSF

Nonfood Compounds

Program Listed (Category E3)

Registration # 144461

Product # 90191120

Net Content 1200 ml (40.6 fl oz)